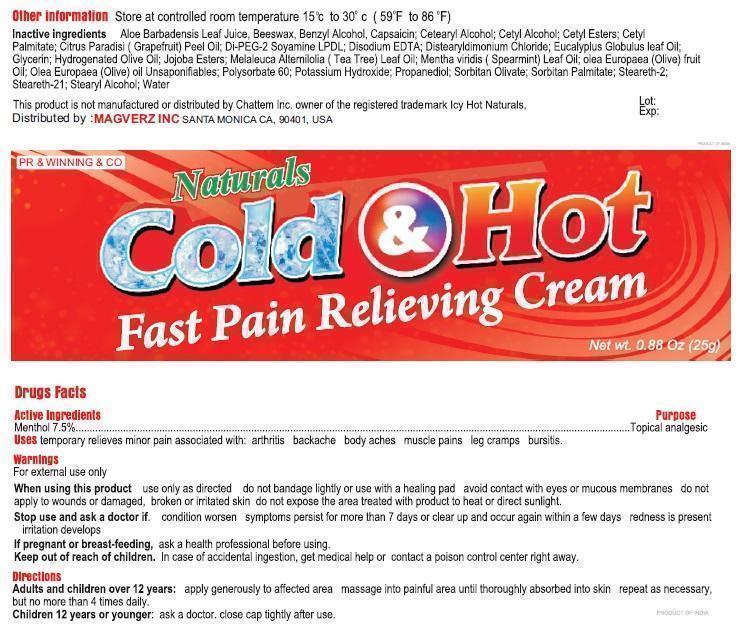 DRUG LABEL: Cold and Hot
NDC: 59240-003 | Form: CREAM
Manufacturer: MAGVERZ INC
Category: otc | Type: HUMAN OTC DRUG LABEL
Date: 20130716

ACTIVE INGREDIENTS: MENTHOL 0.075 g/1 g
INACTIVE INGREDIENTS: ALOE VERA LEAF; YELLOW WAX; BENZYL ALCOHOL; CAPSAICIN; CETOSTEARYL ALCOHOL; CETYL ALCOHOL; CETYL ESTERS WAX; CETYL PALMITATE; CITRUS PARADISI FRUIT OIL; EDETATE DISODIUM; DISTEARYLDIMONIUM CHLORIDE; EUCALYPTUS OIL; GLYCERIN; OLIVE OIL; HYDROLYZED JOJOBA ESTERS (ACID FORM); SPEARMINT; POLYSORBATE 60; POTASSIUM HYDROXIDE; PROPANEDIOL; SORBITAN OLIVATE; PEG-80 SORBITAN PALMITATE; STEARETH-2; STEARETH-21; STEARYL ALCOHOL; WATER

Cold and Hot Cream

Acitves

Menthol 7.5%

Inactives

aloe barbadensis leaf juice, beeswax, benzyl alcohol, capsaicin, cetearyl alcohol, cetyl alcohol, cetyl esters, cetyl palmitate, citrus paradise (grapefruit) peel oil, di-PEG-2 soyamine IPDI, disodium LPDL, distearyldimonium chloride, eucalyptus globules leaf oil, glycerin, hydrogenated olive oil, jojoba esters, melaleuca alternifolia (tea tree) leaf oil, menthe viridis (spearmint) leaf oil, olea europaea (olive) fruit oil, olea europaea (olive) oil unsaponifiables, polysorbate 60, potassium hydroxide, propanediol, sorbitan olivate, sorbitan palmitate, steareth-2, steareth-21, stearyl alcohol, water

Uses

Temporarily relieves minor pain associated with:

arthritis

backache

bodyaches

muscle pains

leg cramps

bursitis

Indication

Temporarily relieves minor pain

Directions

Adults and children over 1 years:apply generously to affected areamassage into painful area until thoroughly absorbed into skinrepeat as necessary, but no more than 4 times daily.

Children 12 years or younger: ask a doctor.

Close cap tighlty after use.

Warnings

For External use only

When using this product

Use only as directed

Do not bandage tightly or with heating pad

Avoid contact with eyes and mucous membranes

Do not apply to wounds or damagged, broken or irritated skin

Do not expose the area treated with product to heat or direct sunlight.

Stop use and ask docotor if;

Condition Worsesns, Symptomps persist for mor than 7 days or clear up and occur again within a few days, Irritation developes.

If pregnant or breast feeding

Ask health professionals before use.

If sollowed get medical help or contact poison control center right away.

Keep Out of Reach of Childrens

Productt Label

Product Label